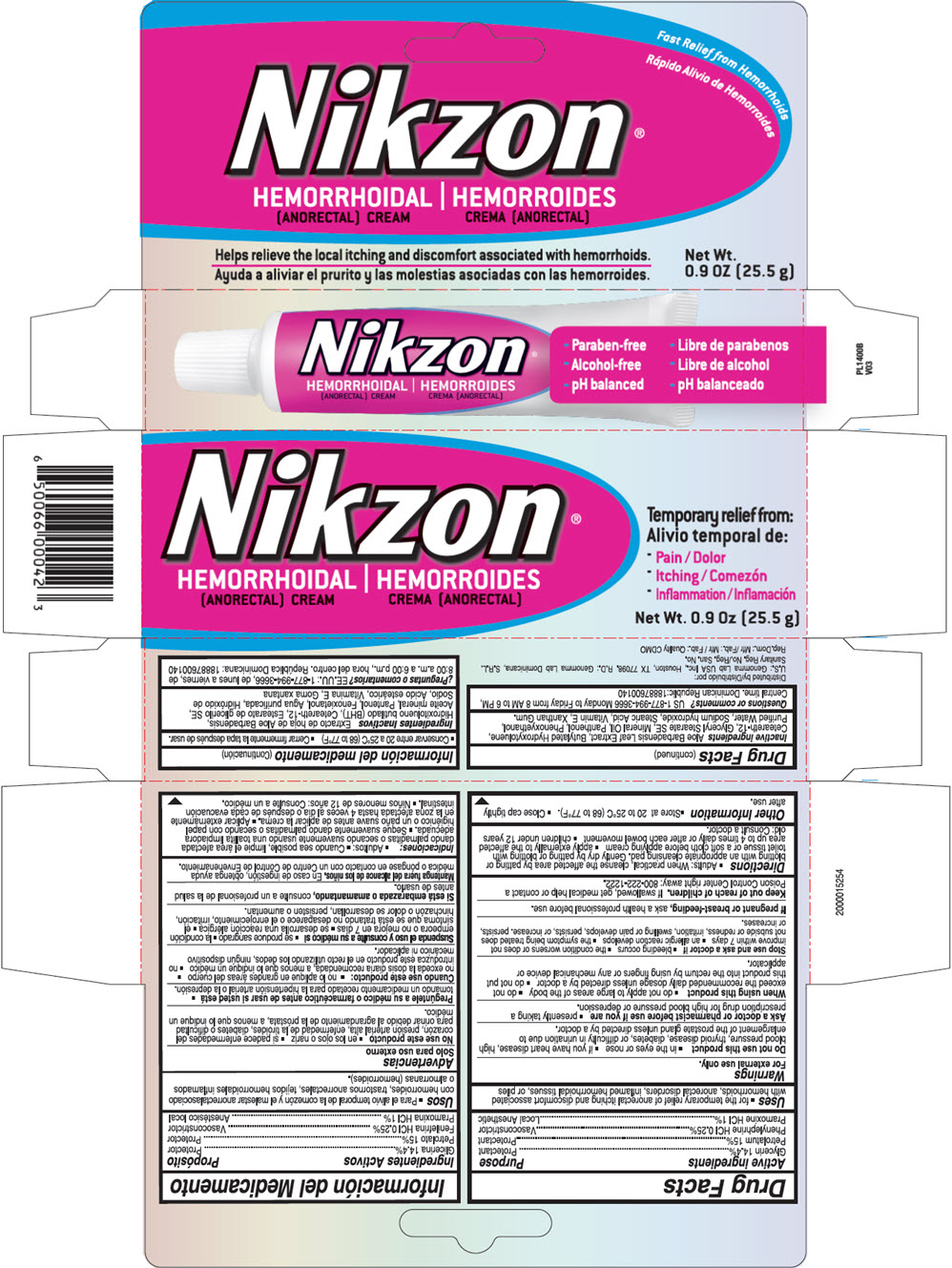 DRUG LABEL: Nikzon Hemorrhoidal
NDC: 50066-010 | Form: CREAM
Manufacturer: Genomma Lab USA
Category: otc | Type: HUMAN OTC DRUG LABEL
Date: 20250714

ACTIVE INGREDIENTS: Glycerin 144 mg/1 g; Petrolatum 150 mg/1 g; Phenylephrine hydrochloride 2.5 mg/1 g; Pramoxine hydrochloride 10 mg/1 g
INACTIVE INGREDIENTS: water; ceteareth-12; glyceryl stearate SE; mineral oil; xanthan gum; stearic acid

Nikzon® Hemorrhoidal Cream

Drug Facts

ACTIVE INGREDIENT

Active ingredients | Purpose
Glycerin 14.4% | Protectant
Petrolatum 15% | Protectant
Phenylephrine HCl 0.25% | Vasoconstrictor
Pramoxine HCl 1% | Local Anesthetic

Uses

- for the temporary relief of anorectal itching and discomfort associated with hemorrhoids, anorectal disorders, inflamed hemorrhoidal tissues, or piles

Warnings

For external use only.

Do not use this product

- in the eyes or nose
- if you have heart disease, high blood pressure, thyroid disease, diabetes, or difficulty in urination due to enlargement of the prostate gland unless directed by a doctor.

Ask a doctor or pharmacist before use if you are

- presently taking a prescription drug for high blood pressure or depression.

When using this product

- do not apply to large areas of the body
- do not exceed the recommended daily dosage unless directed by a doctor
- do not put this product into the rectum by using fingers or any mechanical device or applicator.

Stop use and ask a doctor if

- bleeding occurs
- the condition worsens or does not improve within 7 days
- an allergic reaction develops
- the symptom being treated does not subside or redness, irritation, swelling or pain develops, persists, or increase. persists, or increases.

PREGNANCY OR BREAST FEEDING

If pregnant or breast-feeding, ask a health professional before use.

Keep out of reach of children. If swallowed, get medical help or contact a Poison Control Center right away: 800-222-1222.

Directions

- Adults: When practical, cleanse the affected area by patting or blotting with an appropriate cleansing pad. Gently dry by patting or blotting with toilet tissue or a soft cloth before applying cream
- apply externally to the affected area up to 4 times daily or after each bowel movement
- children under 12 years old: Consult a doctor.

Other Information

- Store at 20 to 25°C (68 to 77°F).
- Close cap tightly after use.

Inactive ingredients

Aloe Barbadensis Leaf Extract, Butylated Hydroxytoluene, Ceteareth-12, Glyceryl Stearate SE, Mineral Oil, Panthenol, Phenoxyethanol, Purified Water, Sodium hydroxide, Stearic Acid, Vitamin E, Xanthan Gum.

Questions or comments?

US 1-877-994-3666 Monday to Friday from 8 AM to 6 PM, Central time. Dominican Republic:18887600140

Distributed by:
U.S.: Genomma Lab USA Inc., Houston, TX 77098.

PRINCIPAL DISPLAY PANEL - 25.5 g Tube Carton

Nikzon®

HEMORRHOIDAL
[ANORECTAL] CREAM

Temporary relief from:

- Pain
- Itching
- Inflammation

Net Wt. 0.9 Oz [25.5 g]